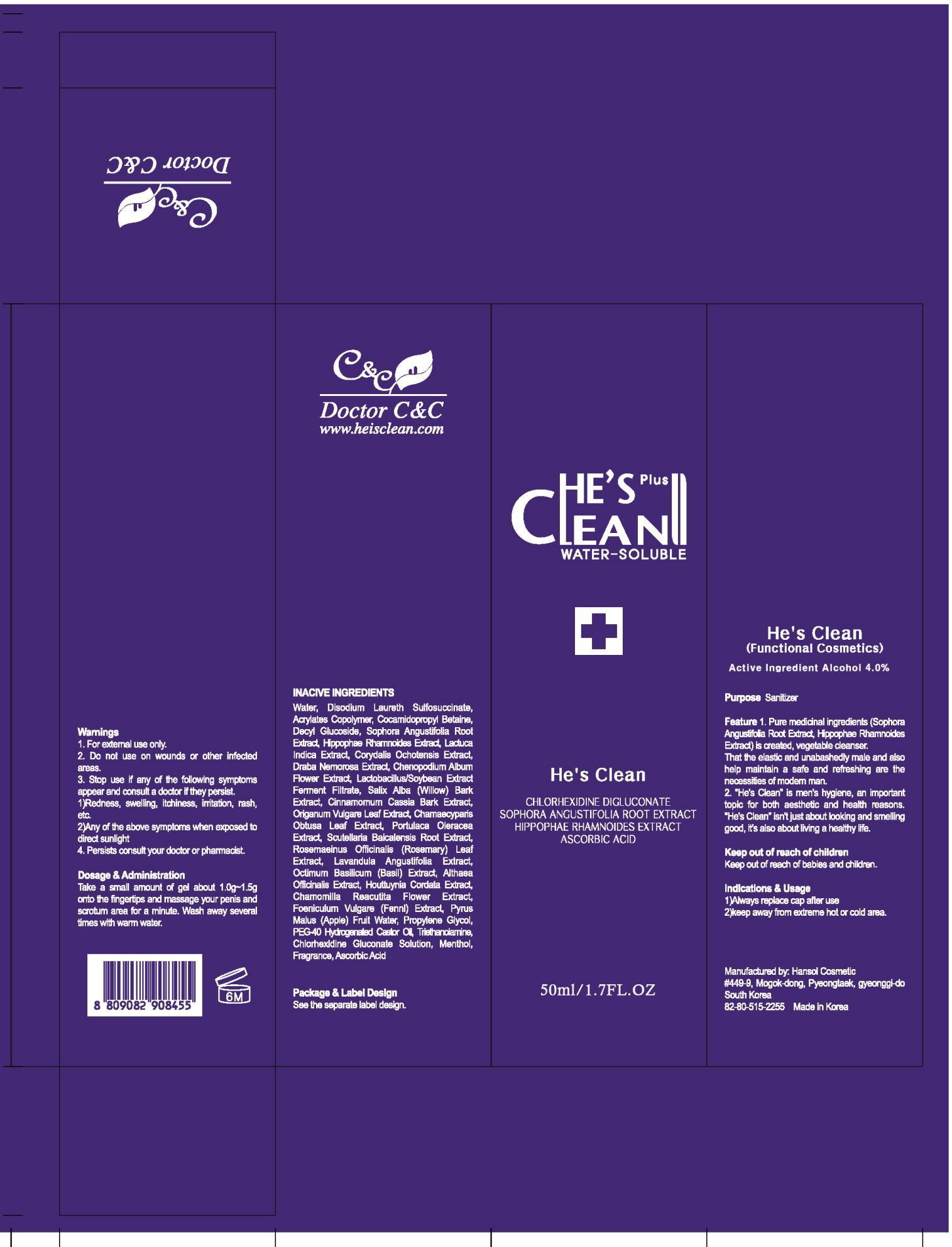 DRUG LABEL: HES CLEAN
NDC: 42979-110 | Form: GEL
Manufacturer: DOCTOR C&C CO., LTD.
Category: otc | Type: HUMAN OTC DRUG LABEL
Date: 20130225

ACTIVE INGREDIENTS: ALCOHOL 4 mg/50 mL
INACTIVE INGREDIENTS: DISODIUM LAURETH SULFOSUCCINATE; WATER; SALIX ALBA BARK

ACTIVE INGREDIENT

Active Ingredient: ALCOHOL 4%

INACTIVE INGREDIENT

Inactive ingredients:
WATER, DISODIUM LAURETH SULFOSUCCINATE, Acrylates Copolymer, Cocamidopropyl Betaine, Decyl Glucoside, Sophora Angustifolia Root Extract, Hippophae Rhamnoides Extract, Lactuca Indica Extract, Corydalis Ochotensis Extract, Draba Nemorosa Extract, Chenopodium Album Flower Extract, Lactobacillus/Soybean Extract Ferment Filtrate, Salix Alba (Willow) Bark Extract, Cinnamomum Cassia Bark Extract, Origanum Vulgare Leaf Extract, Chamaecyparis Obtusa Leaf Extract, Portulaca Oleracea Extract, Scutellaria Baicalensis Root Extract, Rosemarinus Officinalis (Rosemary) Leaf Extract, Lavandula Angustifolia Extract, Octimum Basilicum (Basil) Extract, Althaea Officinalis Extract, Houttuynia Cordata Extract, Chamomilla Reacutita Flower Extract, Foeniculum Vulgare (Fennl) Extract, Pyrus Malus (Apple) Fruit Water, Propylene Glycol, Ethanol, PEG-40 Hydrogenated Castor Oil

PURPOSE

Purpose: Sanitizer

WARNINGS

1. For external use only.
2. Do not use on wounds or other infected areas.
3. Stop use if any of the following symptoms appear and consult a doctor if they persist.
- Redness, swelling, itchiness, irritation, rash, etc.
- Any of the above symptoms when exposed to direct sunlight.
4. Persists consult your doctor or pharmacist.

KEEP OUT OF REACH OF CHILDREN

Keep out of reach of babies and children.

DOSAGE AND ADMINISTRATION

Take a small amount of gel about 1.0g onto the fingertips and massage your penis and scrotum area for a minute. Wash away several times with warm water

INDICATIONS AND USAGE

Indication and usage:
1. Always replace cap after use.
2. Keep away from extreme hot or cold area.